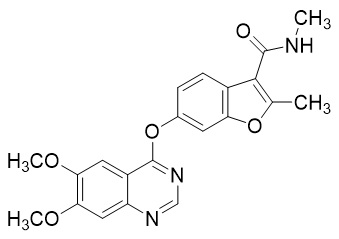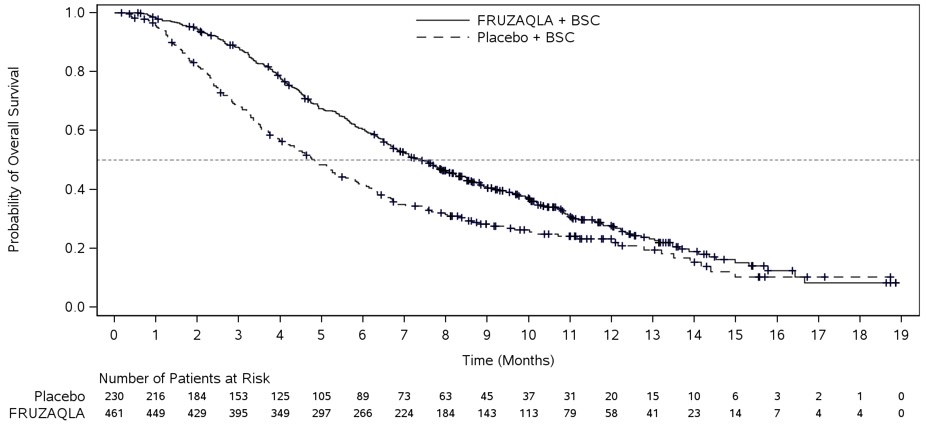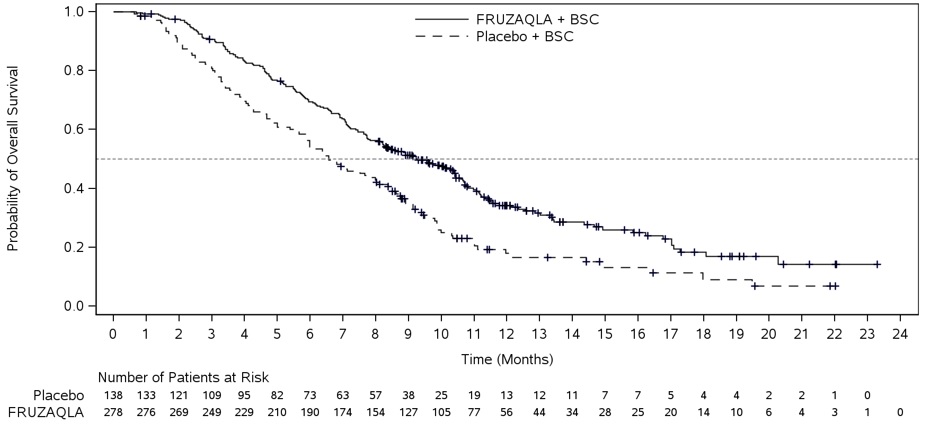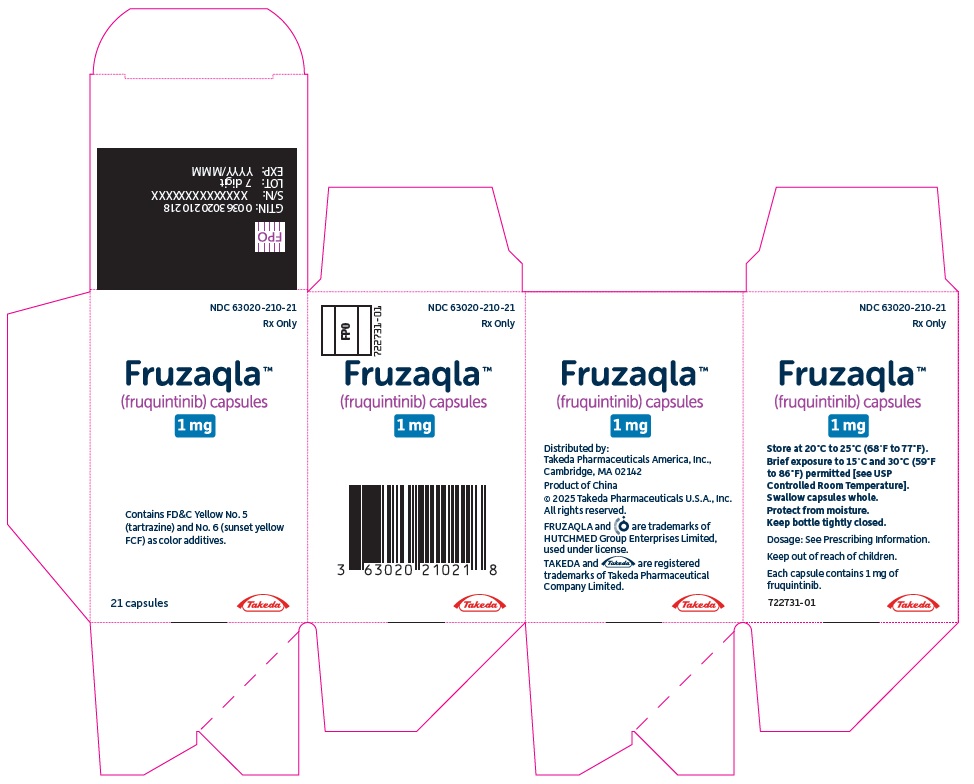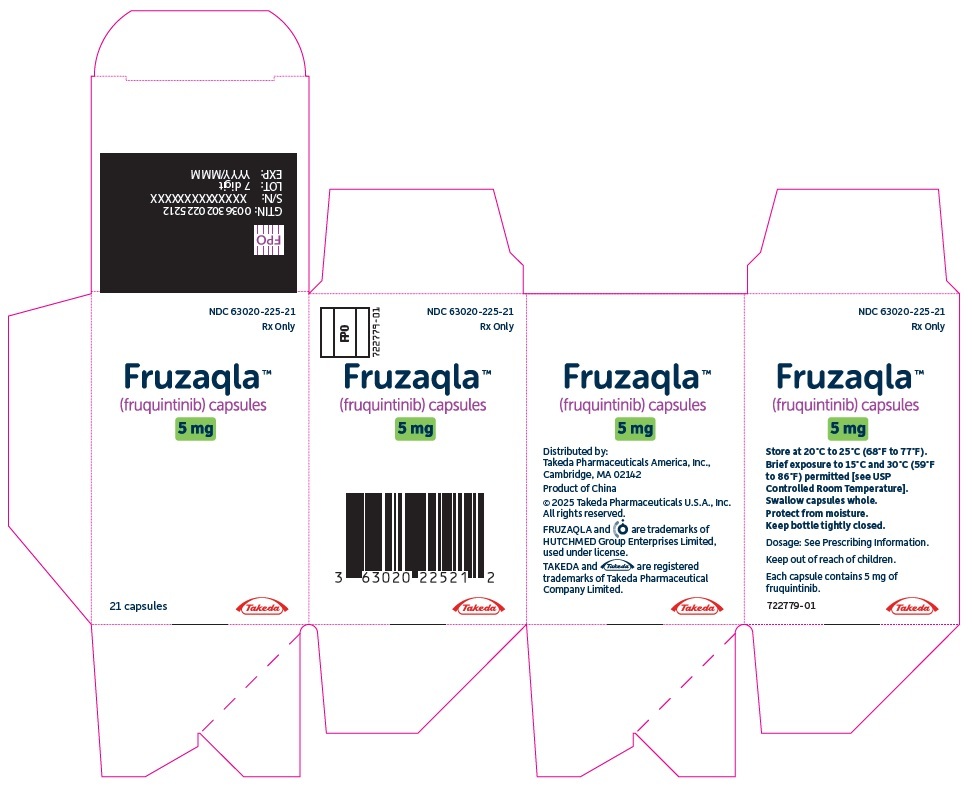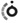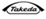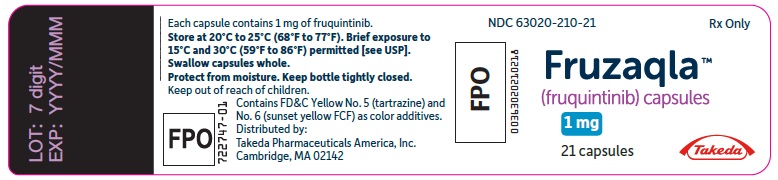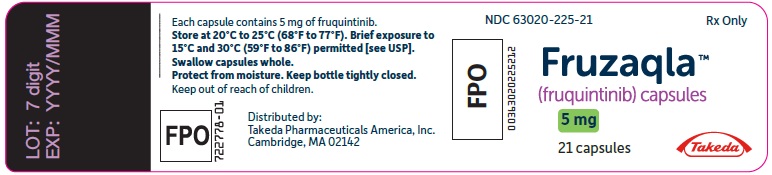 DRUG LABEL: Fruzaqla
NDC: 63020-210 | Form: CAPSULE
Manufacturer: Takeda Pharmaceuticals America, Inc.
Category: prescription | Type: HUMAN PRESCRIPTION DRUG LABEL
Date: 20260205

ACTIVE INGREDIENTS: FRUQUINTINIB 1 mg/1 1
INACTIVE INGREDIENTS: TALC; MICROCRYSTALLINE CELLULOSE; STARCH, CORN; GELATIN, UNSPECIFIED; TITANIUM DIOXIDE; FD&C YELLOW NO. 5; FD&C YELLOW NO. 6

HIGHLIGHTS OF PRESCRIBING INFORMATION

These highlights do not include all the information needed to use FRUZAQLA safely and effectively. See full prescribing information for FRUZAQLA.
FRUZAQLA® (fruquintinib) capsules, for oral use
Initial U.S. Approval: 2023

RECENT MAJOR CHANGES

Dosage and Administration (2.2) | 2/2025

1. INDICATIONS AND USAGE

FRUZAQLA is a kinase inhibitor indicated for the treatment of adult patients with metastatic colorectal cancer (mCRC) who have been previously treated with fluoropyrimidine‑, oxaliplatin‑, and irinotecan‑based chemotherapy, an anti‑VEGF therapy, and, if RAS wild‑type and medically appropriate, an anti-EGFR therapy. (1)

2. DOSAGE AND ADMINISTRATION

The recommended dose of FRUZAQLA is 5 mg orally once daily, with or without food for the first 21 days of each 28-day cycle. (2.1)

3. DOSAGE FORMS AND STRENGTHS

Capsules: 1 mg and 5 mg. (3)

4. CONTRAINDICATIONS

None. (4)

5. WARNINGS AND PRECAUTIONS

- Hypertension: Control blood pressure prior to treatment and monitor during treatment. Manage with anti-hypertensive medications and adjustment of the dose of FRUZAQLA, if necessary. Withhold, dose reduce, or permanently discontinue based on severity of hypertension. (2.2, 5.1)
- Hemorrhagic Events: Closely monitor patients who are at risk for bleeding. Withhold, reduce dose, or permanently discontinue FRUZAQLA based on severity and persistence of hemorrhage. (2.2, 5.2)
- Infections: Monitor for infection during treatment and withhold FRUZAQLA during active infections. Do not start FRUZAQLA in patients with active infections. (5.3)
- Gastrointestinal (GI) Perforation: Periodically monitor for GI perforation. Permanently discontinue FRUZAQLA in patients who develop GI perforation or fistula. (5.4)
- Hepatotoxicity: Monitor liver laboratory tests prior to the start of FRUZAQLA and periodically during treatment. Withhold, reduce the dose, or permanently discontinue based on severity. (2.2, 5.5)
- Proteinuria: Monitor urine protein. Discontinue FRUZAQLA for nephrotic syndrome (2.2, 5.6)
- Palmar-Plantar Erythrodysesthesia: Withhold FRUZAQLA based on severity. (2.2, 5.7)
- Posterior Reversible Encephalopathy Syndrome (PRES): Immediately discontinue FRUZAQLA if PRES is suspected and confirmed via Magnetic Resonance Imaging (MRI). (5.8)
- Impaired Wound Healing: Withhold FRUZAQLA for 2 weeks before major surgery. Do not administer for at least 2 weeks following major surgery and until adequate wound healing. The safety of resumption of FRUZAQLA after resolution of wound healing complications has not been established. (5.9)
- Arterial Thromboembolic Events: Initiation of FRUZAQLA in patients with a recent history of thromboembolic events should be carefully considered. Discontinue FRUZAQLA in patients who develop arterial thromboembolism. (5.10)
- Allergic Reactions to FD&C Yellow No. 5 (Tartrazine) and No. 6 (Sunset Yellow FCF): Contains FD&C Yellow No. 5 (tartrazine) and No. 6 (sunset yellow FCF) as color additives, which may cause allergic reactions (including bronchial asthma) in certain susceptible patients. (5.11)
- Embryo-Fetal Toxicity: Can cause fetal harm. Advise patients of reproductive potential of the potential risk to the fetus and to use effective contraception. (5.12, 8.1, 8.3)

6. ADVERSE REACTIONS

Most common adverse reactions (incidence ≥20%) are hypertension, palmar-plantar erythrodysesthesia, proteinuria, dysphonia, abdominal pain, diarrhea, and asthenia. (6.1)

To report SUSPECTED ADVERSE REACTIONS, contact Takeda Pharmaceuticals America, Inc. at 1-844-662-8532 or FDA at 1-800-FDA-1088 or www.fda.gov/medwatch.

7. DRUG INTERACTIONS

Strong or Moderate CYP3A Inducers: Avoid concomitant use. (7.1)

8. USE IN SPECIFIC POPULATIONS

Lactation: Advise not to breastfeed. (8.2)

FULL PRESCRIBING INFORMATION

1. INDICATIONS AND USAGE

FRUZAQLA is indicated for the treatment of adult patients with metastatic colorectal cancer (mCRC) who have been previously treated with fluoropyrimidine‑, oxaliplatin‑, and irinotecan‑based chemotherapy, an anti‑VEGF therapy, and, if RAS wild‑type and medically appropriate, an anti-EGFR therapy.

2. DOSAGE AND ADMINISTRATION

2.1. Recommended Dosage

The recommended dose of FRUZAQLA is 5 mg orally once daily for the first 21 days of each 28-day cycle until disease progression or unacceptable toxicity. Take FRUZAQLA with or without food [see Clinical Pharmacology (12.3)] at approximately the same time each day.

Swallow the FRUZAQLA capsule whole.

Take a missed dose if less than 12 hours have passed since the missed scheduled dose. Do not take two doses on the same day to make up for a missed dose.

Do not take an additional dose if vomiting occurs after taking FRUZAQLA but continue with the next scheduled dose.

2.2. Dosage Modifications for Adverse Reactions

The recommended dose reductions for adverse reactions are provided in Table 1.

Table 1: Recommended Dose Reductions for FRUZAQLA
Dose Level | FRUZAQLA Dosage
First dose reduction | 4 mg orally once daily
Second dose reduction | 3 mg orally once daily

Permanently discontinue FRUZAQLA in patients unable to tolerate 3 mg orally once daily.

The recommended dosage modifications for adverse reactions are provided in Table 2.

Table 2: Recommended Dosage Modifications for FRUZAQLA
Adverse Reaction | Severity [Severity as defined by National Cancer Institute (NCI) Common Terminology Criteria for Adverse Events (CTCAE) version 5.0.] | FRUZAQLA Dosage Modification
Hypertension [see Warnings and Precautions (5.1)] | Grade 3 | - Withhold FRUZAQLA for Grade 3 hypertension that persists despite optimal anti-hypertensive therapy. - If hypertension fully resolves or recovers to Grade 1, resume at the next lower dose level.
Hypertension [see Warnings and Precautions (5.1)] | Grade 4 | Permanently discontinue FRUZAQLA.
Hemorrhagic Events [see Warnings and Precautions (5.2)] | Grade 2 | - Withhold FRUZAQLA until bleeding fully resolves or recovers to Grade 1. - Resume at the next lower dose level.
Hemorrhagic Events [see Warnings and Precautions (5.2)] | Grade 3 or Grade 4 | Permanently discontinue FRUZAQLA.
Hepatotoxicity [see Warnings and Precautions (5.5)] | Alanine aminotransferase (ALT) or aspartate aminotransferase (AST) greater than 3 times upper limit of normal (ULN), or greater than 3 times baseline if baseline was abnormal; or bilirubin greater than 1.5 times ULN, or greater than 1.5 times baseline if baseline was abnormal | - Withhold FRUZAQLA and monitor AST, ALT and total bilirubin until resolution to Grade 1 or baseline. - Resume at the next lower dose level.
Hepatotoxicity [see Warnings and Precautions (5.5)] | ALT or AST greater than 3 times ULN with concurrent total bilirubin greater than 2 times ULN (in the absence of cholestasis or hemolysis) | Permanently discontinue FRUZAQLA.
Hepatotoxicity [see Warnings and Precautions (5.5)] | AST or ALT greater than 20 times ULN if baseline was normal, or greater than 20 times baseline if baseline was abnormal; or bilirubin greater than 10 times ULN if baseline was normal, or greater than 10 times baseline if baseline was abnormal | Permanently discontinue FRUZAQLA.
Proteinuria [see Warnings and Precautions (5.6)] | 2 grams or greater proteinuria in 24 hours | - Withhold FRUZAQLA until proteinuria fully resolves or is <1 gram/24 hours. - Upon recovery, resume at the next lower dose level.; Permanently discontinue FRUZAQLA for nephrotic syndrome or if proteinuria does not recover to <1 gram/24 hours.
Palmar-plantar erythrodysesthesia (PPE) [see Warnings and Precautions (5.7)] | Grade 2 | - Withhold FRUZAQLA and initiate supportive treatment. - If toxicity fully resolves or recovers to Grade 1, resume at the same dose level.
Palmar-plantar erythrodysesthesia (PPE) [see Warnings and Precautions (5.7)] | Grade 3 | - Withhold FRUZAQLA and initiate supportive treatment. - If toxicity fully resolves or recovers to Grade 1, resume at the next lower dose level.
Other Adverse Reactions [see Adverse Reactions (6.1)] | Grade 3 | - Withhold FRUZAQLA. - If toxicity fully resolves or recovers to Grade 1, resume at the next lower dose level.
Other Adverse Reactions [see Adverse Reactions (6.1)] | Grade 4 | Discontinue FRUZAQLA. Consider resuming FRUZAQLA at the next lower dose level only if the toxicity is non-life threatening and fully resolves or recovers to Grade 1 and the potential benefit outweighs the risks.

3. DOSAGE FORMS AND STRENGTHS

Capsules:

- 1 mg: size 3 hard gelatin capsule with standard yellow opaque cap and white opaque body, imprinted with “HM013” over “1 mg” on the body in black ink.
- 5 mg: size 1 hard gelatin capsule with a red opaque cap and white opaque body, imprinted with “HM013” over “5 mg” on the body in black ink.

4. CONTRAINDICATIONS

None.

5. WARNINGS AND PRECAUTIONS

5.1. Hypertension

FRUZAQLA can cause hypertension. Hypertension occurred in 450 of 911 (49%) patients with mCRC treated with FRUZAQLA, including Grade 3-4 events in 19%, and hypertensive crisis in three patients (0.3%). The median time to first onset of hypertension was 14 days from first dose of FRUZAQLA.

Do not initiate FRUZAQLA unless blood pressure is adequately controlled. Monitor blood pressure weekly the first month, at least monthly thereafter and as clinically indicated. Initiate or adjust anti-hypertensive therapy as appropriate. Withhold, reduce dose, or permanently discontinue FRUZAQLA based on the severity of hypertension [see Dosage and Administration (2.2)].

5.2. Hemorrhagic Events

FRUZAQLA can cause serious hemorrhagic events, which may be fatal. In 911 patients with mCRC treated with FRUZAQLA, 6% of patients experienced a gastrointestinal hemorrhage, including 13 patients (1%) with a Grade ≥3 event and 2 patients with fatal hemorrhages.

Permanently discontinue FRUZAQLA in patients with severe or life-threatening hemorrhage. Monitor the International Normalized Ratio (INR) levels in patients receiving anticoagulants [see Dosage and Administration (2.2)].

5.3. Infections

FRUZAQLA can cause an increased risk of infections, including fatal infections. In 781 patients treated with FRUZAQLA across three randomized, placebo-controlled trials, the overall incidence of infections was higher (18% vs. 12%) including for fatal infections (1% vs. 0.3%) as compared to the placebo arms (n=391).

In 911 patients with mCRC treated with FRUZAQLA, the most common infections were urinary tract infections (6.8%), upper respiratory tract infections (3.2%) and pneumonia (2.5%); fatal infections included pneumonia (0.4%), sepsis (0.2%), bacterial infection (0.1%), lower respiratory tract infection (0.1%), and septic shock (0.1%).

Withhold FRUZAQLA for Grade 3 or 4 infections, or worsening infection of any grade. Resume FRUZAQLA at the same dose when the infection has resolved.

5.4. Gastrointestinal Perforation

FRUZAQLA can cause gastrointestinal perforation. In 911 patients with mCRC treated with FRUZAQLA, 12 patients (1.3%) experienced a Grade ≥3 gastrointestinal perforation, including one fatal event.

Permanently discontinue FRUZAQLA in patients who develop gastrointestinal perforation or fistula.

5.5. Hepatotoxicity

FRUZAQLA can cause liver injury. In 911 patients with mCRC treated with FRUZAQLA, 48% experienced increased ALT or AST, including Grade ≥3 events in 5%, and fatal events in 0.2%. Median time to first onset of elevated liver enzymes was 29 days from first dose of FRUZAQLA.

Monitor liver function tests (ALT, AST, and bilirubin) before initiation and periodically throughout treatment with FRUZAQLA. Temporarily hold and then reduce or permanently discontinue FRUZAQLA depending on the severity and persistence of hepatotoxicity as manifested by elevated liver function tests [see Dosage and Administration (2.2) and Use in Specific Populations (8.6)].

5.6. Proteinuria

FRUZAQLA can cause proteinuria. In 911 patients with mCRC treated with FRUZAQLA, 36% experienced proteinuria and 2.5% of patients experienced Grade ≥3 events. Median time to first onset of proteinuria was 22 days from first dose of FRUZAQLA.

Monitor for proteinuria before initiation and periodically throughout treatment with FRUZAQLA. For proteinuria ≥2 g/24 hours, withhold FRUZAQLA until improvement to ≤Grade 1 proteinuria, resume FRUZAQLA at a reduced dose. Discontinue FRUZAQLA in patients who develop nephrotic syndrome [see Dosage and Administration (2.2)].

5.7. Palmar-Plantar Erythrodysesthesia (PPE)

FRUZAQLA can cause PPE. In 911 patients with mCRC treated with FRUZAQLA, PPE occurred in 35%, including 8% with Grade 3 events. Median time to first onset of PPE was 19 days from first dose of FRUZAQLA.

Based on severity, withhold FRUZAQLA and then resume at the same or reduced dose [see Dosage and Administration (2.2)].

5.8. Posterior Reversible Encephalopathy Syndrome (PRES)

FRUZAQLA can cause PRES, a syndrome of subcortical vasogenic edema diagnosed by characteristic finding on MRI. PRES occurred in one of 911 patients with mCRC treated with FRUZAQLA.

Perform an evaluation for PRES in any patient presenting with seizures, headache, visual disturbances, confusion or altered mental function. Discontinue FRUZAQLA in patients who develop PRES.

5.9. Impaired Wound Healing

Impaired wound healing can occur in patients who receive drugs that inhibit the vascular endothelial growth factor (VEGF) signaling pathway. In 911 patients with mCRC treated with FRUZAQLA, 1 patient experienced a Grade 2 event of wound dehiscence.

Do not administer FRUZAQLA for at least 2 weeks prior to major surgery.

Do not administer FRUZAQLA for at least 2 weeks after major surgery and until adequate wound healing. The safety of resumption of FRUZAQLA after resolution of wound healing complications has not been established.

5.10. Arterial Thromboembolic Events

FRUZAQLA may increase the risk of arterial thromboembolic events. In 911 patients with mCRC treated with FRUZAQLA, 7 patients (0.8%) experienced an arterial thromboembolic event; additionally, FRUZAQLA studies excluded patients with clinically significant cardiovascular disease, uncontrolled hypertension, or with thromboembolic events within the prior 6 months. Initiation of FRUZAQLA in patients with a recent history of thromboembolic events should be carefully considered. In patients who develop arterial thromboembolism discontinue FRUZAQLA.

5.11. Allergic Reactions to FD&C Yellow No. 5 (Tartrazine) and No. 6 (Sunset Yellow FCF)

FRUZAQLA 1 mg capsules contain FD&C Yellow No. 5 (tartrazine), which may cause allergic-type reactions (including bronchial asthma) in certain susceptible persons. Although the overall incidence of FD&C Yellow No. 5 (tartrazine) sensitivity in the general population is low, it is frequently seen in patients who also have aspirin hypersensitivity.

FRUZAQLA 1 mg contains FD&C Yellow No. 6 (sunset yellow FCF), which may cause allergic reactions.

5.12. Embryo-Fetal Toxicity

Based on findings in animal studies and its mechanism of action, FRUZAQLA can cause fetal harm when administered to pregnant women. In an embryo-fetal developmental study in rats, embryotoxic and teratogenic effects were observed at exposures below the clinical exposure [see Use in Specific Populations (8.1)].

Advise pregnant women of the potential risk to a fetus. Advise females of childbearing potential and males with female partners of childbearing potential to use effective contraception during treatment with FRUZAQLA and for 2 weeks after the last dose [see Use in Specific Populations (8.1, 8.3)].

6. ADVERSE REACTIONS

The following clinically significant adverse reactions are described elsewhere in the labeling:

- Hypertension [see Warnings and Precautions (5.1)].
- Hemorrhagic Events [see Warnings and Precautions (5.2)].
- Infections [see Warnings and Precautions (5.3)].
- Gastrointestinal Perforation [see Warnings and Precautions (5.4)].
- Hepatotoxicity [see Warnings and Precautions (5.5)].
- Proteinuria [see Warnings and Precautions (5.6)].
- Palmar-Plantar Erythrodysesthesia (PPE) [see Warnings and Precautions (5.7)].
- Posterior Reversible Encephalopathy Syndrome (PRES) [see Warnings and Precautions (5.8)].

6.1. Clinical Trials Experience

Because clinical trials are conducted under widely varying conditions, adverse reaction rates observed in the clinical trials of a drug cannot be directly compared to rates in the clinical trials of another drug and may not reflect the rates observed in practice.

The pooled safety population described in the WARNINGS AND PRECAUTIONS and below reflects exposure to FRUZAQLA as a single agent in 911 patients with mCRC who were enrolled in three randomized, placebo-controlled studies (FRESCO-2, FRESCO and 2012-013-00CH1) (N=781); three open-label studies (2009-013-00CH1, 2012-013-00CH3 and 2015-013-00US1) (N=124); and an open-label lead-in cohort of FRESCO-2 (N=6). Among the 911 patients who received FRUZAQLA, 23% were exposed for 6 months or longer and 3.5% were exposed for greater than one year. These patients received at least one dose of FRUZAQLA at the recommended dosage of 5 mg daily for the first 21 days of each 28-day cycle. The median age was 60 years (range: 23 to 82) and 34% were 65 years of age or older. The most common adverse reactions (incidence ≥20%) that occurred in pooled monotherapy studies were hypertension, PPE, proteinuria, dysphonia, abdominal pain, diarrhea, and asthenia.

Metastatic Colorectal Cancer
FRESCO-2 Study
The safety of FRUZAQLA was evaluated in FRESCO-2, a randomized, double-blind, placebo-controlled study [see Clinical Studies (14.1)]. Patients received either FRUZAQLA 5 mg daily for the first 21 days of each 28-day cycle plus best supportive care (BSC) (n=456) or matching placebo plus BSC (n=230).

The median duration of therapy with FRUZAQLA was 3 months (range: 0.3 to 19.1 months).

Serious adverse reactions occurred in 38% of patients treated with FRUZAQLA. Serious adverse reactions in ≥2% of patients treated with FRUZAQLA included hemorrhage (2.2%) and gastrointestinal perforation (2.0%). Fatal adverse reaction(s) occurred in 14 (3.1%) patients who received FRUZAQLA. Fatal adverse reactions occurring in ≥2 patients include pneumonia (n=3), sepsis/septic shock (n=2), and hepatic failure/encephalopathy (n=2).

Adverse reactions leading to treatment discontinuation occurred in 20% of patients treated with FRUZAQLA. Adverse reactions leading to treatment discontinuations of FRUZAQLA in ≥1% of patients were asthenia and gastrointestinal perforation.

Dose interruptions of FRUZAQLA due to an adverse reaction occurred in 47% of patients. Adverse reactions leading to dose interruptions of FRUZAQLA in ≥2% of patients were PPE, proteinuria, asthenia, abdominal pain, hypertension, vomiting, and diarrhea.

Dose reductions of FRUZAQLA due to an adverse reaction occurred in 24% of patients. Adverse reactions leading to dose reductions of FRUZAQLA in ≥2% of patients were PPE, hypertension and asthenia.

Table 3 summarizes the adverse reactions in FRESCO-2.

Table 3: Adverse Reactions (≥10%) in Patients who Received FRUZAQLA and with a Difference Between Arms of ≥5% Compared to Placebo in FRESCO-2 (All Grades)
Adverse Reaction | FRUZAQLA (N=456) |  | Placebo (N=230)
 | All Grades (%) | Grade 3 or 4 (%) | All Grades (%) | Grade 3 or 4 (%)
General
Fatigue [Represents a composite of multiple related terms.] | 53 | 12 | 39 | 4.8
Vascular
Hypertension | 38 | 14 | 9 | 0.9
Gastrointestinal
Stomatitis | 31 | 2.2 | 7.8 | 0.4
Abdominal Pain | 25 | 3.5 | 20 | 3
Diarrhea | 24 | 3.7 | 11 | 0
Endocrine Disorders
Hypothyroidism | 21 | 0.4 | 0.4 | 0
Skin and Subcutaneous
Palmar-plantar erythrodysesthesia (hand-foot skin reactions) | 19 | 6 | 2.6 | 0
Renal
Proteinuria | 18 | 1.8 | 5 | 0.9
Respiratory
Dysphonia | 18 | 0 | 5 | 0
Musculoskeletal
Musculoskeletal Pain | 16 | 1.1 | 7 | 0
Arthralgia | 11 | 0.9 | 4.3 | 0

Other important adverse reactions (all grades) that occurred in <10% of patients treated with FRUZAQLA included urinary tract infection (4.6%), epistaxis (3.9%), proctalgia (3.5%), pneumonia (2.4%), gastrointestinal hemorrhage (1.5%), gastrointestinal perforation (1.3%), pancreatitis (0.7%), thrombotic microangiopathy (0.2%), and posterior reversible encephalopathy syndrome (0.2%).

Table 4 provides laboratory abnormalities observed in FRESCO-2.

Table 4: Select Laboratory Abnormalities Worsening from Baseline Occurring in ≥20% of Patients in FRESCO-2
Laboratory [Graded according to NCI CTCAE version 5.0.] Abnormality | FRUZAQLA (N=456) [Each test incidence is based on the number of patients who had both baseline and at least one on-study laboratory measurement available: FRUZAQLA (range: 409-444) and placebo (range: 195-216).] |  | Placebo (N=230)
Laboratory [Graded according to NCI CTCAE version 5.0.] Abnormality | All Grade (%) | Grade 3 or 4 (%) | All Grades (%) | Grade 3 or 4 (%)
Chemistry
Triglycerides Increased | 53 | 2.8 | 22 | 1.0
Cholesterol Increased | 37 | 1.9 | 22 | 1.9
Aspartate Aminotransferase Increased | 36 | 4.3 | 24 | 1.9
Albumin Decreased | 35 | 1.6 | 32 | 1.4
Sodium Decreased | 35 | 1.1 | 27 | 0.9
Alanine Aminotransferase Increased | 34 | 5 | 22 | 1.4
Bilirubin Increased | 30 | 7 | 21 | 8
Alkaline Phosphatase Increased | 20 | 1.6 | 27 | 0.5
Magnesium Decreased | 20 | 0.5 | 10 | 0.5
Hematology
Lymphocytes Decreased | 30 | 6 | 32 | 4.7
Platelets Decreased | 30 | 0.2 | 4.7 | 0
Activated Partial Thromboplastin Time Increased | 21 | 2.7 | 18 | 1.5

Other clinically relevant laboratory abnormalities (all grades) that occurred in <20% of patients treated with FRUZAQLA included pancreatic enzymes increased (3.9%).

FRESCO Study
The safety of FRUZAQLA was evaluated in FRESCO, a randomized, double-blind, placebo-controlled study [see Clinical Studies (14.1)]. Patients received either FRUZAQLA 5 mg daily for the first 21 days of each 28-day cycle plus BSC (n=278) or matching placebo plus BSC (n=137).

The median duration of therapy with FRUZAQLA was 3.68 months (range: 0.3 to 22.1 months).

Serious adverse reactions occurred in 15% of patients treated with FRUZAQLA. Serious adverse reactions in ≥2% of patients included intestinal obstruction (2.9%) and hemorrhage (2.2%). Fatal adverse reaction(s) occurred in 7 (2.5%) patients who received FRUZAQLA including cerebral infarction (n=1), gastrointestinal hemorrhage (n=1), hemoptysis (n=1), bacterial infection (n=1), lung/lower respiratory infection (n=2), and multiple organ dysfunction (n=1).

Adverse reactions leading to treatment discontinuation occurred in 15% of patients who received FRUZAQLA. Adverse reactions leading to treatment discontinuations of FRUZAQLA in ≥1% were intestinal obstruction, proteinuria and hepatic function abnormalities.

Dose interruptions of FRUZAQLA due to an adverse reaction occurred in 35% of patients. Adverse reactions leading to dose interruptions of FRUZAQLA in ≥2% of patients were PPE, proteinuria, platelet count decreased, ALT increased, hypertension, and diarrhea.

Dose reductions of FRUZAQLA due to an adverse reaction occurred in 24% of patients. Adverse reactions leading to dose reduction of FRUZAQLA in ≥2% of patients were PPE, proteinuria, and hypertension.

Table 5 summarizes the adverse reactions in FRESCO.

Table 5: Adverse Reactions (≥10%) in Patients who Received FRUZAQLA and with a Difference Between Arms of ≥5% Compared to Placebo in FRESCO (All Grades)
Adverse Reaction | Fruquintinib (N=278) |  | Placebo (N=137)
Adverse Reaction | All Grades (%) | Grade 3 or 4 (%) | All Grades (%) | Grade 3 or 4 (%)
Vascular
Hypertension [Represents a composite of multiple related terms.] | 61 | 23 | 17 | 2.2
Hemorrhage | 28 | 1.1 | 14 | 0
Renal
Proteinuria | 55 | 4.7 | 30 | 0
Skin and Subcutaneous
Palmar-plantar erythrodysesthesia (hand-foot skin reactions) | 49 | 11 | 2.9 | 0
Respiratory
Dysphonia | 38 | 0 | 1.5 | 0
Throat Pain | 10 | 0 | 1.5 | 0
Gastrointestinal
Stomatitis | 33 | 0.7 | 2.9 | 0
Abdominal Pain | 29 | 4 | 17 | 1.5
Diarrhea | 25 | 3.6 | 5 | 0
General
Fatigue | 25 | 2.5 | 13 | 1.5
Metabolism
Anorexia | 21 | 1.4 | 9 | 0
Musculoskeletal
Musculoskeletal Pain | 22 | 2.2 | 6 | 1.5
Back Pain | 15 | 1.8 | 7 | 0
Arthralgia | 13 | 0.4 | 2.2 | 0
Endocrine Disorders
Hypothyroidism | 17 | 0 | 2.2 | 0

Other clinically important adverse reactions (all grades) that occurred in <10% of patients treated with FRUZAQLA included urinary tract infection (9%), rash (9%), upper respiratory tract infection (4.7%), proctalgia (3.6%), pneumonia (2.9%), and gastrointestinal perforation or fistula (2.2%).

Table 6 provides laboratory abnormalities observed in FRESCO.

Table 6: Select Laboratory Abnormalities Worsening from Baseline Occurring in ≥20% of Patients in FRESCO
Laboratory [Graded according to NCI CTCAE version 4.03.] Abnormality | FRUZAQLA (N=278) [Each test incidence is based on the number of patients who had both baseline and at least one on-study laboratory measurement available: FRUZAQLA (range: 257-277) and placebo (range: 126-134).] |  | Placebo (N=137)
Laboratory [Graded according to NCI CTCAE version 4.03.] Abnormality | All Grades (%) | Grade 3 or 4 (%) | All Grades (%) | Grade 3 or 4 (%)
Chemistry
Creatinine Increased | 87 | 0.7 | 75 | 1.5
Glucose Increased | 43 | 1.1 | 31 | 3.0
Aspartate Aminotransferase Increased | 42 | 3.6 | 31 | 1.5
Alkaline Phosphatase Increased | 40 | 4.3 | 34 | 6
Bilirubin Increased | 39 | 4.7 | 34 | 8
Alanine Aminotransferase Increased | 33 | 2.2 | 18 | 1.5
Sodium Decreased | 33 | 6 | 31 | 5
Urate Increased | 26 | 26 | 22 | 22
Calcium Decreased | 25 | 0.4 | 13 | 0
Potassium Decreased | 22 | 1.8 | 15 | 2.3
Hematology
Platelets Decreased | 29 | 3.6 | 6 | 0.7
Hemoglobin Decreased | 23 | 0.7 | 33 | 4.5

Other clinically relevant laboratory abnormalities (all grades) that occurred in <20% of patients treated with FRUZAQLA included pancreatic enzymes increased (4.3%).

7. DRUG INTERACTIONS

7.1. Effects of Other Drugs on FRUZAQLA

Strong CYP3A Inducers

Avoid concomitant use of drugs that are strong CYP3A inducers with FRUZAQLA.

Concomitant use with a strong CYP3A inducer may decrease fruquintinib Cmax and AUC [see Clinical Pharmacology (12.3)], which may reduce the efficacy of FRUZAQLA.

Moderate CYP3A Inducers

If possible, avoid concomitant use of drugs that are moderate CYP3A inducers with FRUZAQLA. If it is not possible to avoid concomitant use of a moderate CYP3A inducer and fruquintinib, continue to administer FRUZAQLA at the recommended dosage.

Concomitant use with a moderate CYP3A inducer may decrease fruquintinib Cmax and AUC [see Clinical Pharmacology (12.3)], which may reduce the efficacy of FRUZAQLA.

8. USE IN SPECIFIC POPULATIONS

8.1. Pregnancy

Risk Summary

Based on findings in animal studies and its mechanism of action, FRUZAQLA can cause fetal harm when administered to a pregnant woman. In an embryo-fetal developmental study in pregnant rats, oral administration of fruquintinib during the period of organogenesis resulted in teratogenicity and embryo lethality at exposures below the clinical exposure (see Data). There are no data on the use of FRUZAQLA in pregnant women. Advise pregnant women of the potential risk to a fetus.

In the U.S. general population, the estimated background risk of major birth defects and miscarriage in clinically recognized pregnancies is 2 to 4% and 15 to 20%, respectively.

Data

Animal Data

In an embryo-fetal developmental study in pregnant rats, daily oral administration of fruquintinib at doses ≥0.1 mg/kg [approximately 0.2 times the recommended clinical dose of 5 mg based on body surface area (BSA)] during the period of organogenesis resulted in fetal external (edema and head and tail abnormalities), visceral, and skeletal malformations. At doses of 0.25 mg/kg (approximately 0.5 times the recommended clinical dose of 5 mg based on BSA), an increase in post-implantation loss and reduction in live fetuses was observed.

8.2. Lactation

Risk Summary

There are no data regarding the presence of fruquintinib or its metabolites in human milk or its effects on a breastfed child or on milk production. Because of the potential for serious adverse reactions in the breastfed child, advise women not to breastfeed during treatment with FRUZAQLA and for 2 weeks after the last dose.

8.3. Females and Males of Reproductive Potential

Pregnancy Testing

Verify pregnancy status of females of reproductive potential prior to initiating FRUZAQLA.

Contraception

Females and Males

Females of childbearing potential and males with female partners of childbearing potential should use effective contraception during treatment and for 2 weeks after the last dose of FRUZAQLA [see Warnings and Precautions (5.11) and Nonclinical Toxicology (13.1)].

Infertility

Females and Males

There are no data on the effects of fruquintinib on human fertility. Based on findings in animal studies, FRUZAQLA may impair female fertility [see Nonclinical Toxicology (13.1)].

8.4. Pediatric Use

The safety and efficacy of FRUZAQLA in patients younger than 18 years of age have not been established.

8.5. Geriatric Use

In FRESCO-2, 212 (46%) patients who received FRUZAQLA were ≥65 years of age and older, of whom 43 (20%) of patients were ≥75 years. There were no observed overall differences in safety and effectiveness of FRUZAQLA in geriatric compared to younger patients.

Of the total number of FRUZAQLA-treated patients in the FRESCO study, 50 (18%) were 65 years of age and older, and one patient was ≥75 years. There were no observed overall differences in safety and effectiveness of FRUZAQLA in geriatric compared to younger patients.

8.6. Hepatic Impairment

No dosage adjustment is recommended for patients with mild hepatic impairment (total bilirubin less than or equal to the ULN with AST greater than ULN or total bilirubin greater than 1 to 1.5 times ULN with any AST [see Clinical Pharmacology (12.3)].

FRUZAQLA has not been sufficiently studied in patients with moderate hepatic impairment (total bilirubin greater than 1.5 times and less than 3 times ULN and any AST). FRUZAQLA is not recommended for use in patients with severe hepatic impairment (total bilirubin greater than 3 times ULN and any AST).

11. DESCRIPTION

Fruquintinib is a kinase inhibitor with the chemical name 6-[(6,7-dimethoxyquinazolin-4-yl)oxy]-N,2-dimethyl-1-benzofuran-3-carboxamide. Its molecular formula is C21H19N3O5, which corresponds to a molecular weight of 393.39 g/mol. Fruquintinib has the following chemical structure:

Fruquintinib is a white to off-white powder with a dissociation constant (pKa) of 2.78. The aqueous solubility of fruquintinib is pH-dependent with a solubility of 0.9 μg/mL at pH 6.8 that increases under acidic conditions to 129.9 μg/mL at pH 1.

FRUZAQLA (fruquintinib) capsules for oral administration contain 1 mg or 5 mg of fruquintinib. The inactive ingredients are corn starch, microcrystalline cellulose, and talc. The 1 mg capsule shell contains FD&C Yellow No. 5 (tartrazine), FD&C Yellow No. 6 (sunset yellow FCF), gelatin, and titanium dioxide. The 5 mg capsule shell contains FD&C Blue No. 1 (brilliant blue FCF), FD&C Red No. 40 (allura red AC), gelatin, and titanium dioxide. The printing ink for 1 mg and 5 mg capsules contains butanol, dehydrated alcohol, ferrosoferric oxide, isopropyl alcohol, potassium hydroxide, propylene glycol, purified water, shellac and strong ammonia solution.

12. CLINICAL PHARMACOLOGY

12.1. Mechanism of Action

Fruquintinib is a small molecule kinase inhibitor of vascular endothelial growth factor receptors (VEGFR)-1, -2, and -3 with IC50 values of 33, 35, and 0.5 nM, respectively. In vitro studies showed fruquintinib inhibited VEGF-mediated endothelial cell proliferation and tubular formation. In vitro and in vivo studies showed fruquintinib inhibited VEGF-induced VEGFR-2 phosphorylation. In vivo studies showed fruquintinib inhibited tumor growth in a tumor xenograft mouse model of colon cancer.

12.2. Pharmacodynamics

Fruquintinib exposure-response relationships and the time course of pharmacodynamic response are unknown.

Cardiac Electrophysiology

A mean increase in QTc interval >20 milliseconds (ms) was not observed at the approved recommended dosage.

12.3. Pharmacokinetics

The fruquintinib steady-state geometric mean (% coefficient of variation [CV]) maximum concentration (Cmax) is 300 ng/mL (28%) and area under the concentration-time curve for the dosing interval (AUC0-24h) is 5880 ng∙h/mL (29%) at the recommended dosage. The fruquintinib Cmax and AUC0-24h are dose-proportional across the dosage range of 1 to 6 mg (0.2 to 1.2 times the recommended dosage). Fruquintinib steady state is achieved after 14 days with a mean AUC0-24h accumulation of 4-fold.

Absorption

The fruquintinib median (min, max) time to Cmax is approximately 2 hours (0, 26 hours).

Effect of Food

No clinically significant differences in fruquintinib pharmacokinetics were observed following administration of a high-fat meal (800 to 1000 calories, 50% fat).

Distribution

The mean (SD) apparent volume of distribution of fruquintinib is approximately 46 (13) L. Plasma protein binding of fruquintinib is approximately 95%.

Elimination

The fruquintinib mean (SD) elimination half-life is approximately 42 (11) hours and the apparent clearance is 14.8 (4.4) mL/min.

Metabolism

Fruquintinib is primarily eliminated by CYP450 and non-CYP450 (i.e., sulfation and glucuronidation) metabolism. CYP3A and to a lesser extent CYP2C8, CYP2C9, and CYP2C19 are the CYP450 enzymes involved in fruquintinib metabolism.

Excretion

Following oral administration of a 5 mg radiolabeled fruquintinib dose, approximately 60% of the dose was recovered in urine (0.5% unchanged) and 30% of the dose was recovered in feces (5% unchanged).

Specific Populations

No clinically significant differences in the pharmacokinetics of fruquintinib were observed based on age (18 to 82 years), sex, race (Asian, Black, and White), ethnicity (Hispanic/Latino vs. non-Hispanic/Latino), body weight (48 to 108 kg), mild to severe renal impairment (CLcr 15 to 89 mL/min estimated by the Cockcroft-Gault equation), mild hepatic impairment (total bilirubin less than or equal to ULN with AST greater than ULN or total bilirubin greater than 1 to 1.5 times ULN with any AST).

The effect of moderate to severe hepatic impairment (total bilirubin greater than 1.5 times ULN and any AST) on fruquintinib pharmacokinetics is unknown.

Drug Interaction Studies

Clinical Studies and Model-Informed Approaches

Strong CYP3A inducers: Fruquintinib Cmax decreased by 12% and AUCinf by 65% following concomitant use with rifampin (strong CYP3A inducer).

Moderate CYP3A inducers: Fruquintinib Cmax is predicted to decrease by 4% and AUCinf by 32% following concomitant use with efavirenz (moderate CYP3A inducer).

Other Drugs: No clinically significant differences in fruquintinib pharmacokinetics were observed when used concomitantly with itraconazole (strong CYP3A inhibitor) or rabeprazole (proton pump inhibitor; gastric acid reducing agent).

No clinically significant differences in the pharmacokinetics of the following drugs were observed when used concomitantly with fruquintinib: dabigatran etexilate (P-gp substrate), or rosuvastatin (BCRP substrate).

In Vitro Studies

Cytochrome P450 Enzymes: Fruquintinib is not an inhibitor of CYP1A2, CYP2B6, CYP2C8, CYP2C9, CYP2C19, CYP2D6 and CYP3A, or an inducer of CYP1A2, CYP2B6, CYP3A.

Transporter Systems: Fruquintinib is not a substrate of P-glycoprotein (P-gp), organic anion transporting polypeptide (OATP)1B1 or OATP1B3. Fruquintinib is not an inhibitor of OATP1B1, OATP1B3, organic anion transporter (OAT)1, OAT3, organic cation transporter (OCT)2, multidrug and toxin extrusion protein (MATE)1, or MATE2-K.

13. NONCLINICAL TOXICOLOGY

13.1. Carcinogenesis, Mutagenesis, Impairment of Fertility

Carcinogenicity studies have not been conducted with fruquintinib.

Fruquintinib was not mutagenic in the in vitro bacterial reverse mutation (Ames) assay or clastogenic in the in vitro Chinese hamster ovary chromosome aberration assay. Fruquintinib was not genotoxic in the in vivo rat micronucleus or alkaline comet assays.

In a fertility and early embryonic development study in rats, post-implantation loss was observed at doses approximately equal to the recommended clinical dose of 5 mg based on BSA.

13.2. Animal Toxicology and/or Pharmacology

In repeat dose toxicity studies in rats, daily oral administration of fruquintinib at doses ≥0.6 mg/kg (approximately 1.2 times the recommended clinical dose of 5 mg based on BSA) resulted in broken or lost teeth.

14. CLINICAL STUDIES

14.1. Metastatic Colorectal Cancer

FRESCO-2 Study

The efficacy of FRUZAQLA was evaluated in FRESCO-2 (NCT04322539), an international, multicenter, randomized, double-blind, placebo-controlled study that enrolled 691 patients with metastatic colorectal cancer who had disease progression during or after prior treatment with fluoropyrimidine-, oxaliplatin-, irinotecan-based chemotherapy, an anti-VEGF biological therapy, if RAS wild type, an anti-EGFR biological therapy, and trifluridine/tipiracil, regorafenib, or both. Patients with an ECOG PS ≥2, left ventricular fraction ≤50%, systolic blood pressure >140 mm Hg or diastolic blood pressure >90 mm Hg, urine protein ≥1 g/24h, or untreated brain metastases were ineligible. Randomization was stratified by prior use of trifluridine/tipiracil or regorafenib (trifluridine/tipiracil vs. regorafenib vs. trifluridine/tipiracil and regorafenib), RAS status (wild type vs. mutant), and duration of metastatic disease (≤18 months vs. >18 months).

Patients were randomized (2:1) to receive FRUZAQLA 5 mg orally once daily (N=461) for the first 21 days of each 28-day cycle plus BSC or placebo (N=230) plus BSC. Patients received either FRUZAQLA or placebo until disease progression or unacceptable toxicity. The major efficacy outcome measure was overall survival (OS) and an additional efficacy outcome measure was progression-free survival (PFS) as determined by investigators according to RECIST v1.1.

The study population characteristics were median age of 64 years (range: 25 to 86), with 47% ≥65 years of age; 56% male; 81% White, 9% Asian, 2.9% Black or African American, and 0.7% Native Hawaiian/Pacific Islander; 43% had an ECOG PS of 0 and 57% had an ECOG PS of 1, and 63% had RAS-mutant tumors. Eighteen percent of the patients were enrolled in North America, 72% in Europe, and 10% in Asia Pacific (Japan and Australia) region.

All patients received prior treatment with fluoropyrimidine, oxaliplatin, and irinotecan-based chemotherapy; 96% received prior anti-VEGF therapy, 39% received prior anti-EGFR therapy, 91% received trifluridine/tipiracil, 48% received regorafenib, and 39% received both trifluridine/tipiracil and regorafenib.

The addition of FRUZAQLA to BSC resulted in a statistically significant improvement in OS and PFS compared to placebo plus BSC (see Table 7, Figure 1).

FRESCO Study

The efficacy of FRUZAQLA was evaluated in FRESCO (NCT02314819), a multicenter, randomized, double-blind, placebo-controlled study conducted in China that enrolled 416 patients with metastatic colorectal cancer who had disease progression during or after prior treatment with fluoropyrimidine-, oxaliplatin, or irinotecan-based chemotherapy. Patients older than 75 years of age, Eastern Cooperative Oncology Group (ECOG) performance status (PS) ≥2, left ventricular ejection fraction ≤50%, systolic blood pressure >140 mm Hg or diastolic blood pressure >90 mm Hg, urine protein ≥1 g/24h, or brain metastases were ineligible. Randomization was stratified by prior use of VEGF inhibitors (yes vs. no) and K-RAS status (wild type vs. mutant).

Patients were randomized (2:1) to receive FRUZAQLA 5 mg orally once daily (N=278) for the first 21 days of each 28-day cycle plus BSC or placebo (N=138) plus BSC. Patients received either FRUZAQLA or placebo until disease progression or unacceptable toxicity. The major efficacy outcome measure was OS and an additional efficacy outcome measure was PFS as determined by investigators according to RECIST v1.1.

The study population characteristics were median age of 56 years (range: 23 to 75), with 19% ≥65 years of age; 61% male; 100% Asian; 27% had an ECOG PS of 0 and 73% had an ECOG PS of 1 (73%), and 44% had K-RAS mutant tumors.

All patients received prior treatment with fluoropyrimidine-, oxaliplatin- and irinotecan-based chemotherapy; 30% of patients received prior anti-VEGF therapy, and 14% received prior anti-EGFR therapy.

The addition of FRUZAQLA to BSC resulted in a statistically significant improvement in OS compared to placebo plus BSC (see Table 7, Figure 2).

Table 7: Efficacy Results from FRESCO-2 and FRESCO Studies
 | FRESCO-2 |  | FRESCO
Endpoint | FRUZAQLA + BSC N=461 | Placebo + BSC N=230 | FRUZAQLA + BSC N=278 | Placebo + BSC N=138
OS
Number of patients with event (%) | 317 (69%) | 173 (75%) | 188 (68%) | 109 (79%)
Median in months (95% CI) | 7.4 (6.7, 8.2) | 4.8 (4.0, 5.8) | 9.3 (8.2, 10.5) | 6.6 (5.9, 8.1)
Hazard Ratio [The Hazard Ratio and its 95% CI were estimated using a stratified Cox proportional hazards model.] (95% CI) | 0.66 (0.55, 0.80) |  | 0.65 (0.51, 0.83)
P-Value [P-Value (2-sided) was calculated using a stratified log-rank test.] | <0.001 |  | <0.001
PFS
Number of patients with event (%) | 392 (85%) | 213 (93%) | 235 (85%) | 125 (91%)
Median in months (95% CI) | 3.7 (3.5, 3.8) | 1.8 (1.8, 1.9) | 3.7 (3.7,4.6) | 1.8 (1.8, 1.8)
Hazard Ratio (95% CI) | 0.32 (0.27, 0.39) |  | 0.26 (0.21, 0.34)
P-Value [P-Value for the PFS analysis in FRESCO was not included due to lack of multiplicity adjustment for this analysis.] | <0.001 |  | -
Abbreviations: CI=confidence interval; N=number of patients; OS=overall survival; PFS=progression-free survival

Figure 1: Kaplan-Meier Curve for Overall Survival in FRESCO-2

Figure 2: Kaplan-Meier Curve for Overall Survival in FRESCO

16. HOW SUPPLIED/STORAGE AND HANDLING

How Supplied

Capsule Strength | Description | Package Configuration | NDC Number
1 mg | Size 3 hard gelatin capsule with yellow opaque cap and white opaque body, imprinted with “HM013” over “1 mg” on the body in black ink | White high-density polyethylene (HDPE) bottle with child-resistant closure packaged in a carton. Each bottle contains 21 capsules. | 63020-210-21
5 mg | Size 1 hard gelatin capsule with a red opaque cap and white opaque body, imprinted with “HM013” over “5 mg” on the body in black ink | White high-density polyethylene (HDPE) bottle with child-resistant closure packaged in a carton. Each bottle contains 21 capsules. | 63020-225-21

Storage and handling

Store at 20°C to 25°C (68°F to 77°F). Brief exposure to 15°C and 30°C (59°F to 86°F) permitted (see USP Controlled Room Temperature).

Any unused medicinal product or waste material should be disposed of in accordance with local requirements.

17. PATIENT COUNSELING INFORMATION

Advise the patient to read the FDA-approved patient labeling (Patient Information).

Hypertension

Advise patients to undergo regular blood pressure monitoring and to contact their health care provider if blood pressure is elevated or if symptoms from hypertension occur including severe headache, lightheadedness, or new neurologic symptoms [see Warnings and Precautions (5.1)].

Hemorrhages

Advise patients that FRUZAQLA may increase the risk of bleeding and to contact their healthcare provider for unusual, severe, or persistent bleeding, bruising, or symptoms of bleeding, such as lightheadedness [see Warnings and Precautions (5.2)].

Infections

Advise patients to contact their healthcare provider if they experience signs and symptoms of infection [see Warnings and Precautions (5.3)].

Gastrointestinal Perforation

Advise patients to contact a healthcare provider immediately if they experience severe abdominal pains, or other symptoms of gastrointestinal perforation or fistula [see Warnings and Precautions (5.4)].

Hepatotoxicity

Advise patients that they will need to undergo laboratory tests to monitor liver function and to report any new symptoms indicating hepatic toxicity or failure [see Warnings and Precautions (5.5)].

Proteinuria

Advise patients that they will need to undergo laboratory tests to monitor for proteinuria and to contact their healthcare provider for signs or symptoms of proteinuria [see Warnings and Precautions (5.6)].

Palmar-plantar erythrodysesthesia (PPE)

Advise patients to contact their healthcare provider for progressive or intolerable rash [see Warnings and Precautions (5.7)].

Posterior Reversible Encephalopathy Syndrome (PRES)

Advise patients to immediately contact their healthcare provider for new onset or worsening neurological function [see Warnings and Precautions (5.8)].

Impaired Wound Healing

Advise patients that FRUZAQLA may impair wound healing. Advise patients to inform their healthcare provider of any planned surgical procedure [see Warnings and Precautions (5.9)].

Arterial Thrombosis

Advise patients to seek immediate medical attention for new onset chest pain or acute neurologic symptoms consistent with myocardial infarction or stroke [see Warnings and Precautions (5.10)].

Allergic Reactions to FD&C Yellow No. 5 (Tartrazine) and No. 6 (Sunset Yellow FCF)

Advise patients that FRUZAQLA 1 mg contains FD&C Yellow No. 5 (tartrazine), which may cause allergic-type reactions (including bronchial asthma) in certain susceptible persons or in patients who also have aspirin hypersensitivity [see Warnings and Precautions (5.11)].

Advise patients FRUZAQLA 1 mg contains FD&C Yellow No. 6 (sunset yellow FCF) which may cause allergic-type reactions [see Warnings and Precautions (5.11)].

Embryo-Fetal Toxicity

Advise females to inform their healthcare provider if they are pregnant or become pregnant. Inform females of the risk to a fetus and potential loss of pregnancy [see Warnings and Precautions (5.12) and Use in Specific Populations (8.1)].

Advise females of reproductive potential to use effective contraception during treatment and for 2 weeks after the last dose of FRUZAQLA [see Warnings and Precautions (5.12) and Use in Specific Populations (8.3)].

Advise males with female partners of reproductive potential to use effective contraception during treatment and for 2 weeks following the last dose of FRUZAQLA [see Warnings and Precautions (5.11) and Use in Specific Populations (8.3)].

Lactation

Advise patients not to breastfeed during treatment with FRUZAQLA and for 2 weeks after the last dose of FRUZAQLA [see Use in Specific Populations (8.2)].

Infertility

Advise females of reproductive potential that FRUZAQLA may cause post-implantation loss [see Use in Specific Populations (8.3), Nonclinical Toxicology (13.1)].

Distributed by:
Takeda Pharmaceuticals America, Inc.
Cambridge, MA 02142

FRUZAQLA and are trademarks of HUTCHMED Group Enterprises Limited, used under license.

TAKEDA and are registered trademarks of Takeda Pharmaceutical Company Limited.

©2025 Takeda Pharmaceuticals U.S.A., Inc. All rights reserved.

FRU380 R2

PATIENT INFORMATION
FRUZAQLA® (fru-zahk-la)
(fruquintinib)
capsules

What is FRUZAQLA?

FRUZAQLA is a prescription medicine used to treat adults with colon or rectal cancer that has spread to other parts of the body (metastatic colorectal cancer [mCRC]) and who have received previous treatment with certain anti-cancer medicines.
It is not known if FRUZAQLA is safe and effective in children.

Before taking FRUZAQLA, tell your healthcare provider about all of your medical conditions, including if you:

- have high blood pressure.
- have bleeding problems.
- have an infection.
- have liver or kidney problems.
- plan to have surgery or have had recent surgery. You should stop taking FRUZAQLA at least 2 weeks before your planned surgery. Your healthcare provider will tell you when you can start FRUZAQLA again after your surgery. See “What are the possible side effects of FRUZAQLA?”
- have recently had a blood clot, stroke, or heart attack.
- are allergic to FD&C Yellow No. 5 (tartrazine) or FD&C Yellow No. 6 (sunset yellow FCF). See “What are the possible side effects of FRUZAQLA?”
- are pregnant or plan to become pregnant. FRUZAQLA can harm your unborn baby. You should not become pregnant during treatment with FRUZAQLA.
  Females who can become pregnant:
  - Your healthcare provider will do a pregnancy test before you start treatment with FRUZAQLA.
  - Use effective birth control (contraception) during treatment and for 2 weeks after your last dose of FRUZAQLA.
  - Tell your healthcare provider right away if you become pregnant during treatment with FRUZAQLA.
  Males with female partners who can become pregnant:
  - Use effective birth control during treatment and for 2 weeks after your last dose of FRUZAQLA.
  - Tell your healthcare provider right away if your partner becomes pregnant during your treatment with FRUZAQLA.
- are breastfeeding or plan to breastfeed. It is not known if FRUZAQLA passes into your breast milk. Do not breastfeed during treatment and for 2 weeks after your last dose of FRUZAQLA.

Tell your healthcare provider about all the medicines you take, including prescription and over-the-counter medicines, vitamins, and herbal supplements. FRUZAQLA may affect the way other medicines work, and other medicines may affect how FRUZAQLA works.
Especially tell your healthcare provider if you take blood thinners (anticoagulants).
Know the medicines you take. Keep a list of your medicines to show to your healthcare provider and pharmacist when you get a new medicine.

How should I take FRUZAQLA?

- Take FRUZAQLA exactly as your healthcare provider tells you.
- Your healthcare provider may change your dose, temporarily stop, or permanently stop treatment with FRUZAQLA if you have certain side effects. Do not change your dose or stop taking FRUZAQLA unless your healthcare provider tells you.
- You will usually take FRUZAQLA 1 time a day for 21 days (3 weeks) and then stop for 7 days (1 week). This is 1 cycle of treatment. Repeat this cycle for as long as your healthcare provider tells you.
- Take FRUZAQLA about the same time each day with or without food and swallow the capsule whole.
- If you miss a dose of FRUZAQLA, you can take the missed dose within 12 hours on the same day. If more than 12 hours have passed, take your regularly scheduled dose the next day at the usual time. Do not take 2 doses at the same time to make up for the missed dose.
- Do not take another dose if you vomit after taking FRUZAQLA. Take your regularly scheduled dose the next day at the usual time.
- If you take too much FRUZAQLA, call your healthcare provider or go to the nearest hospital emergency room right away.

What are the possible side effects of FRUZAQLA?
FRUZAQLA may cause serious side effects, including:

- High blood pressure (hypertension). High blood pressure is common with FRUZAQLA and can also be severe. Your healthcare provider will check your blood pressure before starting treatment with FRUZAQLA, 1 time every week for the first month of treatment, and then at least 1 time a month or more often if needed during treatment. Your healthcare provider may prescribe medicine to treat your high blood pressure if needed. Tell your healthcare provider if you get any of the following symptoms of hypertension during treatment:

- severe headache
- lightheadedness or dizziness
- confusion
- changes in vision

- chest pain
- trouble breathing
- nosebleeds
- vomiting

- Severe bleeding (hemorrhage). FRUZAQLA can cause bleeding that can be serious and may lead to death. Tell your healthcare provider if you get any of the following symptoms of bleeding during treatment:

- unusual, severe, or bleeding that will not stop
- bruising
- lightheadedness
- vomiting blood or your vomit looks like coffee grinds
- blood in the stool or black stool that looks like tar

- blood in the urine or urine that looks red, pink or brown
- coughing up blood or blood clots
- menstrual bleeding that is heavier than normal
- unusual vaginal bleeding
- nose bleeds that happen often

- Infections. FRUZAQLA can increase the risk of infections, including serious infections that can lead to death. The most common infections with FRUZAQLA happened in the urinary tract, nose or throat, and lungs. Tell your healthcare provider if you get any of the following symptoms of infection during treatment:

- fever
- severe cough with or without an increase in mucus (sputum) production
- severe sore throat

- trouble breathing
- burning or pain when you urinate
- redness, swelling or pain in any part of the body

- A tear in your stomach or intestinal wall (gastrointestinal perforation). FRUZAQLA can cause gastrointestinal perforation that can be serious and may lead to death. Tell your healthcare provider right away, if you get any of the following symptoms of gastrointestinal perforation during treatment:

- severe stomach (abdominal) pain or stomach pain that does not go away
- vomiting or vomiting blood

- blood in the stool or black stool that looks like tar
- fever or chills
- nausea

- Liver problems. Increased liver enzymes in your blood are common with FRUZAQLA and can also be severe and may lead to death. Your healthcare provider will do blood tests before and during treatment with FRUZAQLA to check for liver problems. Tell your healthcare provider if you get any of the following symptoms of liver problems during treatment:

- yellowing of your skin or the white part of your eyes
- dark colored (tea colored) urine
- pain in your right upper stomach-area (abdomen)

- loss of appetite
- nausea or vomiting
- bleeding or bruising

- Protein in your urine (proteinuria). Protein in your urine is common with FRUZAQLA and can also be severe. Your healthcare provider will check your urine for protein before starting and during treatment with FRUZAQLA. Tell your healthcare provider if you have to urinate more than usual, or if you get swelling of your face, hands, arms, legs, or feet during treatment.

- Hand-foot skin reactions (Palmar-Plantar Erythrodysesthesia [PPE]). Hand-foot skin reactions are common with FRUZAQLA and can also be severe. Tell your healthcare provider if you get a severe rash or redness, pain, blisters, bleeding, or swelling on the palms of your hands or soles of your feet during treatment.

- Posterior Reversible Encephalopathy Syndrome (PRES). PRES is a serious condition that can happen in your brain during treatment with FRUZAQLA. Tell your healthcare provider right away if you get any of the following symptoms during treatment:

- headache
- seizures
- confusion

- changes in vision
- problems thinking

- Wound healing problems. Wounds may not heal properly during treatment with FRUZAQLA. Tell your healthcare provider if you plan to have any surgery before starting FRUZAQLA or during treatment.

- You should stop taking FRUZAQLA at least 2 weeks before planned surgery.
- Your healthcare provider will tell you when you may start taking FRUZAQLA again after surgery.

- Blood clots in your blood vessels (arteries). FRUZAQLA can cause blood clots or blockage in your blood vessels that may lead to heart attack, stroke, or death. Get medical help right away if you get any of the following symptoms during treatment:

- severe chest pain or pressure
- pain in your arms, legs, back, neck or jaw
- shortness of breath
- numbness or weakness of your face, arm, or leg, especially on one side of your body
- feeling lightheaded or faint
- sweating more than usual

- sudden confusion, trouble talking, or understanding things
- trouble walking
- sudden severe headache
- sudden vision changes in one or both eyes
- dizziness, or loss of balance or coordination

- Allergic reactions to FD&C Yellow No. 5 and FD&C Yellow No. 6. FRUZAQLA 1 mg capsules contain the inactive ingredients FD&C Yellow No. 5 (tartrazine) and FD&C Yellow No. 6 (sunset yellow FCF). FD&C Yellow No. 5 (tartrazine) can cause allergic-type reactions (including bronchial asthma) in certain people, especially people who also have an allergy to aspirin. FD&C Yellow No. 6 (sunset yellow FCF) can also cause allergic reactions. Tell your healthcare provider if you get hives, rash, or trouble breathing during treatment with FRUZAQLA.

The most common side effects of FRUZAQLA include:

- voice changes or hoarseness
- stomach-area (abdominal) pain

- diarrhea
- weakness, lack of strength and energy, and feeling very tired or sleepy (asthenia)

FRUZAQLA may cause fertility problems in females, which may affect your ability to have children. Talk to your healthcare provider if you have concerns about fertility.
These are not all of the possible side effects of FRUZAQLA. Call your doctor for medical advice about side effects. You may report side effects to FDA at 1-800-FDA-1088.

How should I store FRUZAQLA?

- Store FRUZAQLA at room temperature between 68°F to 77°F (20°C to 25°C).
- Keep FRUZAQLA dry and away from moisture.
- The FRUZAQLA bottle comes with a child resistant closure.
- Safely throw away (discard of) any unused FRUZAQLA.

Keep FRUZAQLA and all medicines out of the reach of children.

General information about the safe and effective use of FRUZAQLA.
Medicines are sometimes prescribed for purposes other than those listed in a Patient Information leaflet. Do not use FRUZAQLA for a condition for which it was not prescribed. Do not give FRUZAQLA to other people, even if they have the same symptoms that you have. It may harm them. You can ask your pharmacist or healthcare provider for information about FRUZAQLA that is written for health professionals.

What are the ingredients in FRUZAQLA?
Active ingredient: fruquintinib
Inactive ingredients: corn starch, microcrystalline cellulose, talc
Capsule shell:

- 1 mg capsule: FD&C Yellow No. 5 (tartrazine), FD&C Yellow No. 6 (sunset yellow FCF), gelatin, and titanium dioxide
- 5 mg capsule: FD&C Blue No. 1 (brilliant blue FCF), FD&C Red No. 40 (allura red AC), gelatin, and titanium dioxide

Printing ink: butanol, dehydrated alcohol, ferrosoferric oxide, isopropyl alcohol, potassium hydroxide, propylene glycol, purified water, shellac, and strong ammonia solution.

Distributed by:
Takeda Pharmaceuticals America, Inc.
Cambridge, MA 02142
FRUZAQLA and are trademarks of HUTCHMED Group Enterprises Limited, used under license.
TAKEDA and are registered trademarks of Takeda Pharmaceutical Company Limited.
©2025 Takeda Pharmaceuticals U.S.A., Inc. All rights reserved.
For more information, go to www.fruzaqla.com or call 1-844-217-6468.
FRU380 R2

This Patient Information has been approved by the U.S. Food and Drug Administration.

Revised: 2/2025

PRINCIPAL DISPLAY PANEL - 1 mg Capsules

NDC 63020-210-21

Rx Only

Fruzaqla™
(fruquintinib) capsules

1 mg

Contains FD&C Yellow No. 5
(tartrazine) and No. 6 (sunset yellow
FCF) as color additives.

21 capsules

Takeda

PRINCIPAL DISPLAY PANEL - 1 mg Capsules Label

NDC 63020-210-21

Rx Only

Fruzaqla™
(fruquintinib) capsules

1 mg

21 capsules

Takeda

PRINCIPAL DISPLAY PANEL - 5 mg Capsules

NDC 63020-225-21

Rx Only

Fruzaqla™
(fruquintinib) capsules

5 mg

21 capsules

Takeda

PRINCIPAL DISPLAY PANEL - 5 mg Capsules Label

NDC 63020-225-21

Rx Only

Fruzaqla™
(fruquintinib) capsules

5 mg

21 capsules

Takeda